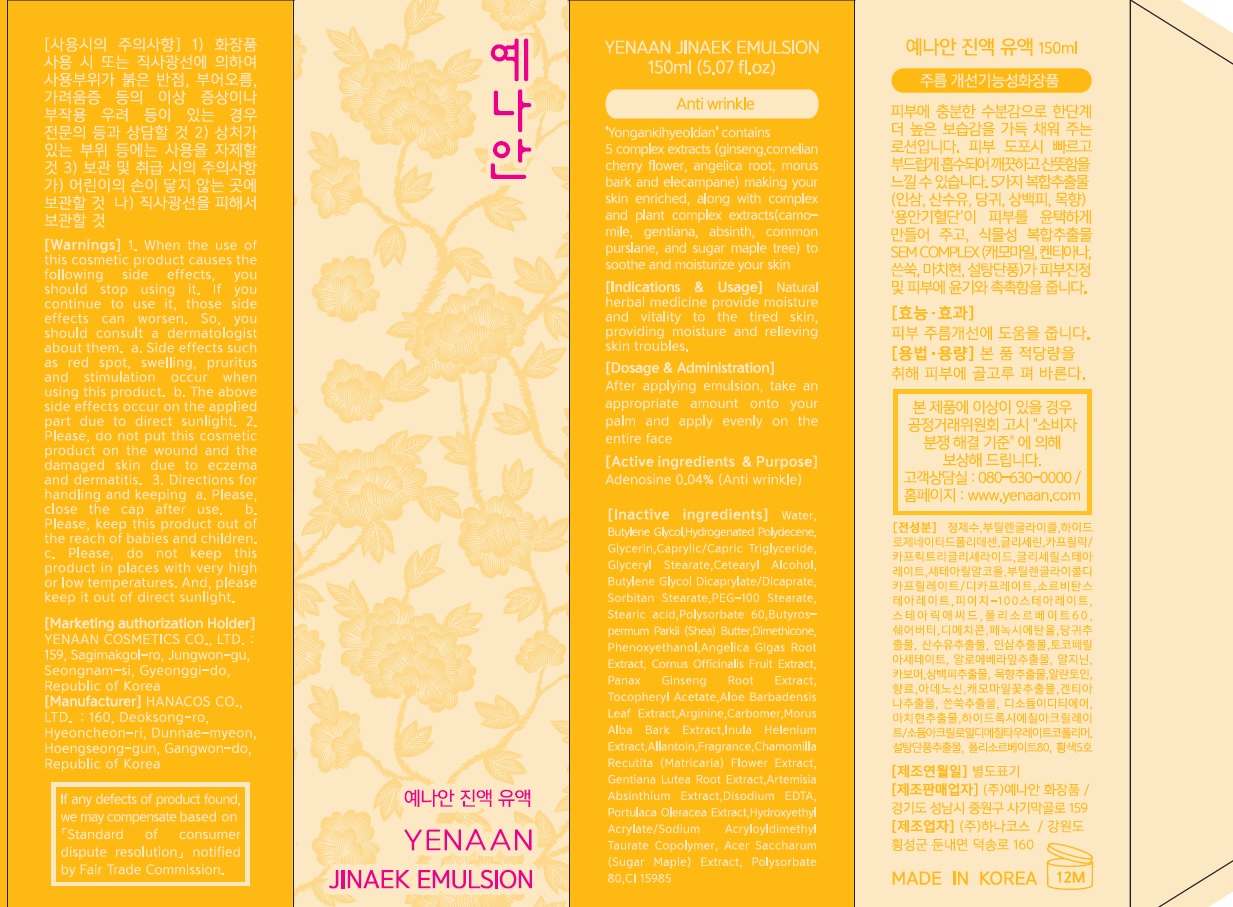 DRUG LABEL: YENAAN JINAEK
NDC: 71195-040 | Form: EMULSION
Manufacturer: YENAAN COSMETICS
Category: otc | Type: HUMAN OTC DRUG LABEL
Date: 20170328

ACTIVE INGREDIENTS: Adenosine 0.06 g/150 mL
INACTIVE INGREDIENTS: Water; Butylene Glycol

ACTIVE INGREDIENT

Active ingredients: Adenosine 0.04%

INACTIVE INGREDIENT

Inactive ingredients: Water, Butylene Glycol, Hydrogenated Polydecene, Glycerin, Cetearyl Alcohol, Caprylic/Capric Triglyceride, Glyceryl Stearate, Butylene Glycol Dicaprylate/Dicaprate, Sorbitan Stearate, PEG-100 Stearate, Stearic acid, Polysorbate 60, Butyrospermum Parkii (Shea) Butter, Dimethicone, Arginine, Carbomer, Hydroxyethyl Acrylate/Sodium Acryloyldimethyl Taurate Copolymer, Angelica Gigas Root Extract, Cornus Officinalis Fruit Extract, Panax Ginseng Root Extract, Tocopheryl Acetate, Aloe Barbadensis Leaf Extract, Morus Alba Bark Extract, Inula Helenium Extract, Allantoin, Chamomilla Recutita (Matricaria) Flower Extract, Gentiana Lutea Root Extract, Artemisia Absinthium Extract, Disodium EDTA, Polysorbate 80, Portulaca Oleracea Extract, Acer Saccharum (Sugar Maple) Extract, Phenoxyethanol, Fragrance, CI 15985

PURPOSE

Purpose: Anti wrinkle

WARNINGS

Warnings: 1. When the use of this cosmetic product causes the following side effects, you should stop using it. If you continue to use it, those side effects can worsen. So, you should consult a dermatologist about them. a. Side effects such as red spot, swelling, pruritus and stimulation occur when using this product. b. The above side effects occur on the applied part due to direct sunlight. 2. Please, do not put this cosmetic product on the wound and the damaged skin due to eczema and dermatitis. 3. Directions for handling and keeping a. Please, close the cap after use. b. Please, keep this product out of the reach of babies and children. c. Please, do not keep this product in places with very high or low temperatures. And, please keep it out of direct sunlight.

KEEP OUT OF REACH OF CHILDREN

Please, keep this product out of the reach of babies and children.

INDICATIONS & USAGE

Indications & Usage: Natural herbal medicine provide moisture and vitality to the tired skin, providing moisture and relieving skin troubles.

DOSAGE & ADMINISTRATION

Dosage & Administration: After applying emulsion, take an appropriate amount onto your palm and apply evenly on the entire face